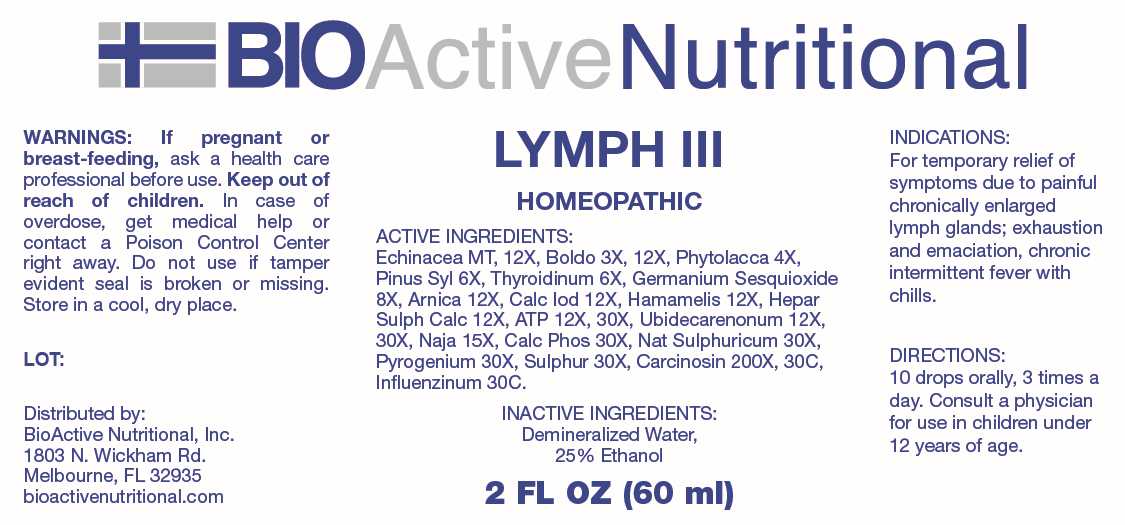 DRUG LABEL: Lymph
NDC: 43857-0641 | Form: LIQUID
Manufacturer: BioActive Nutritional, Inc.
Category: homeopathic | Type: HUMAN OTC DRUG LABEL
Date: 20250516

ACTIVE INGREDIENTS: ECHINACEA ANGUSTIFOLIA WHOLE 1 [hp_X]/1 mL; PEUMUS BOLDUS LEAF 3 [hp_X]/1 mL; PHYTOLACCA AMERICANA ROOT 4 [hp_X]/1 mL; PINUS SYLVESTRIS LEAFY TWIG 6 [hp_X]/1 mL; THYROID 6 [hp_X]/1 mL; GERMANIUM SESQUIOXIDE 8 [hp_X]/1 mL; ARNICA MONTANA WHOLE 12 [hp_X]/1 mL; CALCIUM IODIDE 12 [hp_X]/1 mL; HAMAMELIS VIRGINIANA ROOT BARK/STEM BARK 12 [hp_X]/1 mL; CALCIUM SULFIDE 12 [hp_X]/1 mL; ADENOSINE TRIPHOSPHATE DISODIUM 12 [hp_X]/1 mL; UBIDECARENONE 12 [hp_X]/1 mL; NAJA NAJA VENOM 15 [hp_X]/1 mL; TRIBASIC CALCIUM PHOSPHATE 30 [hp_X]/1 mL; SODIUM SULFATE 30 [hp_X]/1 mL; RANCID BEEF 30 [hp_X]/1 mL; SULFUR 30 [hp_X]/1 mL; HUMAN BREAST TUMOR CELL 300 [hp_X]/1 mL; INFLUENZA A VIRUS WHOLE 30 [hp_C]/1 mL; INFLUENZA A VIRUS A/DARWIN/6/2021 (H3N2) WHOLE 30 [hp_C]/1 mL; INFLUENZA B VIRUS B/AUSTRIA/1359417/2021 BVR-26 WHOLE 30 [hp_C]/1 mL; INFLUENZA B VIRUS B/PHUKET/3073/2013 BVR-1B WHOLE 30 [hp_C]/1 mL
INACTIVE INGREDIENTS: WATER; ALCOHOL

DRUG FACTS:

ACTIVE INGREDIENTS:

Echinacea 1X, 12X, Boldo 3X, 12X, Phytolacca Decandra 4X, Pinus Sylvestris 6X, Thyroidinum 6X, Germanium Sesquioxide 8X, Arnica Montana 12X, Calcarea Iodata 12X, Hamamelis Virginiana 12X, Hepar Sulphuris Calcareum 12X, Adenosinum Triphosphoricum Dinatrum 12X, 30X, Ubidecarenonum 12X, 30X, Naja Tripudians 15X, Calcarea Phosphorica 30X, Natrum Sulphuricum 30X, Pyrogenium 30X, Sulphur 30X, Carcinosin 200X, 30C, Influenzinum 30C.

PURPOSE:

For temporary relief of symptoms due to painful chronically enlarged lymph glands; exhaustion and emaciation, chronic intermittent fever with chills.

WARNINGS:

If pregnant or breast-feeding, ask a health care professional before use.

Keep out of reach of children. In case of overdose, get medical help or contact a Poison Control Center right away.

Do not use if tamper evident seal is broken or missing.

Store in a cool, dry place.

KEEP OUT OF REACH OF CHILDREN:

In case of overdose, get medical help or contact a Poison Control Center right away.

DIRECTIONS:

10 drops orally, 3 times a day. Consult a physician for use in children under 12 years of age.

INDICATIONS:

For temporary relief of symptoms due to painful chronically enlarged lymph glands; exhaustion and emaciation, chronic intermittent fever with chills.

INACTIVE INGREDIENTS:

Demineralized Water, 25% Ethanol

QUESTIONS:

Distributed by:

BioActive Nutritional, Inc.

1803 N. Wickham Rd.

Melbourne, FL 32935

bioactivenutritional.com

PACKAGE LABEL DISPLAY:

BIOActive Nutritional

LYMPH III

HOMEOPATHIC

2 FL OZ (60 ml)